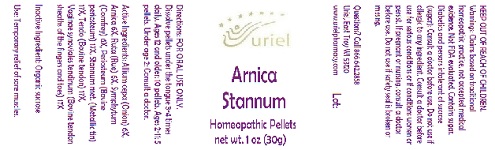 DRUG LABEL: Arnica Stannum
NDC: 48951-1158 | Form: PELLET
Manufacturer: Uriel Pharmacy Inc.
Category: homeopathic | Type: HUMAN OTC DRUG LABEL
Date: 20180531

ACTIVE INGREDIENTS: ONION 6 [hp_X]/1 1; ARNICA MONTANA 6 [hp_X]/1 1; RUTA GRAVEOLENS FLOWERING TOP 6 [hp_X]/1 1; COMFREY ROOT 6 [hp_X]/1 1; BOS TAURUS BONE 17 [hp_X]/1 1; TIN 17 [hp_X]/1 1; BOS TAURUS TENDON 17 [hp_X]/1 1
INACTIVE INGREDIENTS: SUCROSE

Arnica Stannum

INDICATIONS AND USAGE

Directions: FOR ORAL USE ONLY.

DOSAGE AND ADMINISTRATION

Dissolve pellets under the tongue 3-4 times daily. Ages 12 and older: 10 pellets. Ages 2-11: 5 pellets. Under age 2: Consult a doctor.

ACTIVE INGREDIENT

Active Ingredients: Allium cepa (Onion) 6X, Arnica 6X, Ruta (Rue) 6X, Symphytum (Comfrey) 6X, Periosteum (Bovine periosteum) 17X, Stannum met. (Metallic tin) 17X, Tendo (Bovine tendon) 17X,
Vaginae synoviales tendinum (Bovine tendon sheaths of the fingers and toes) 17X

Inactive Ingredient: Sucrose

PURPOSE

Use: Temporary relief of sore muscles.

KEEP OUT OF REACH OF CHILDREN.

WARNINGS

Warnings: Claims based on traditional homeopathic practice, not accepted medical evidence. Not FDA evaluated. Contains sugar. Diabetics and persons intolerant of sucrose (sugar): Consult a doctor before use. Do not use if allergic to any ingredient. Consult a doctor before use for serious conditions or if conditions worsen or persist. If pregnant or nursing, consult a doctor before use. Do not use if safety seal is broken or missing.

Questions? Call 866.642.2858
Uriel, East Troy WI 53120
www.urielpharmacy.com